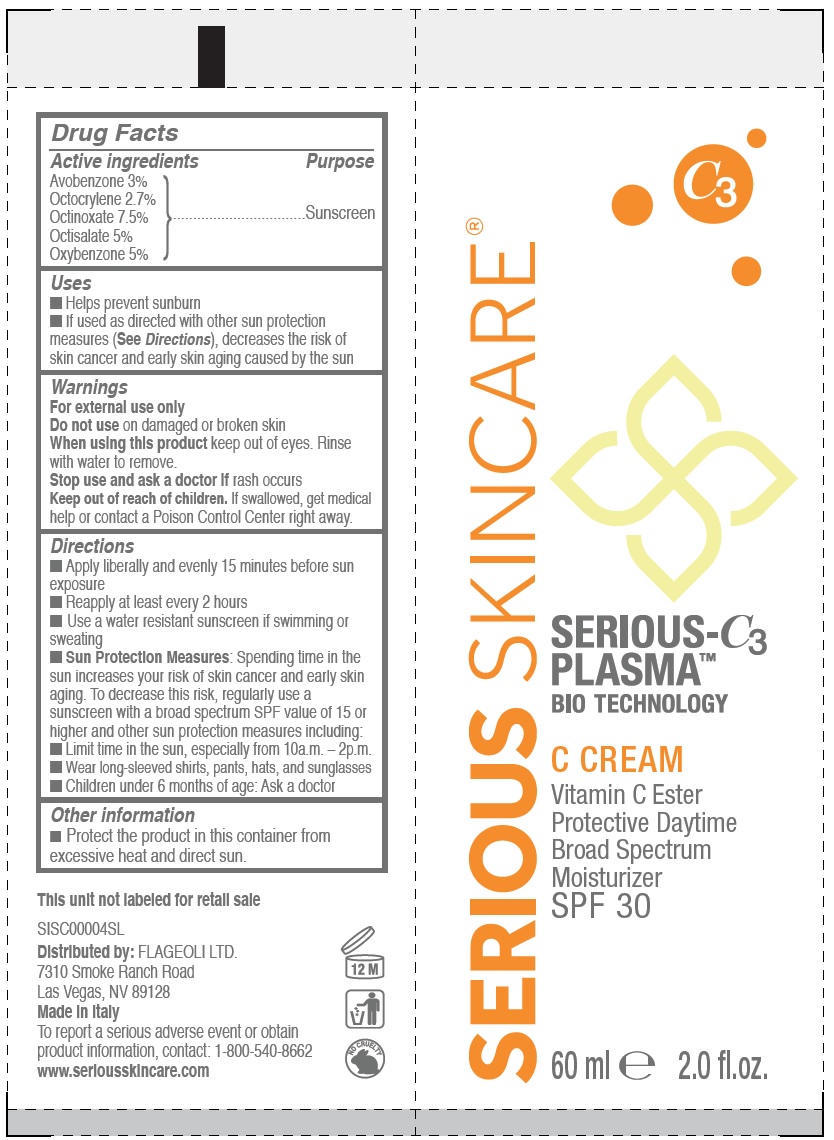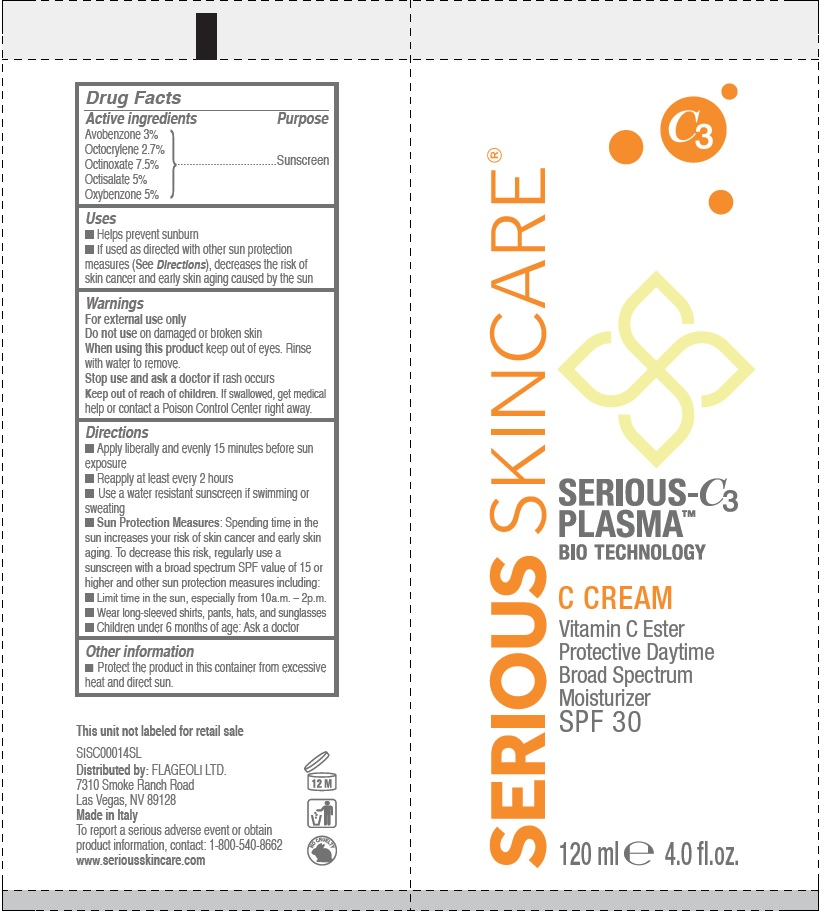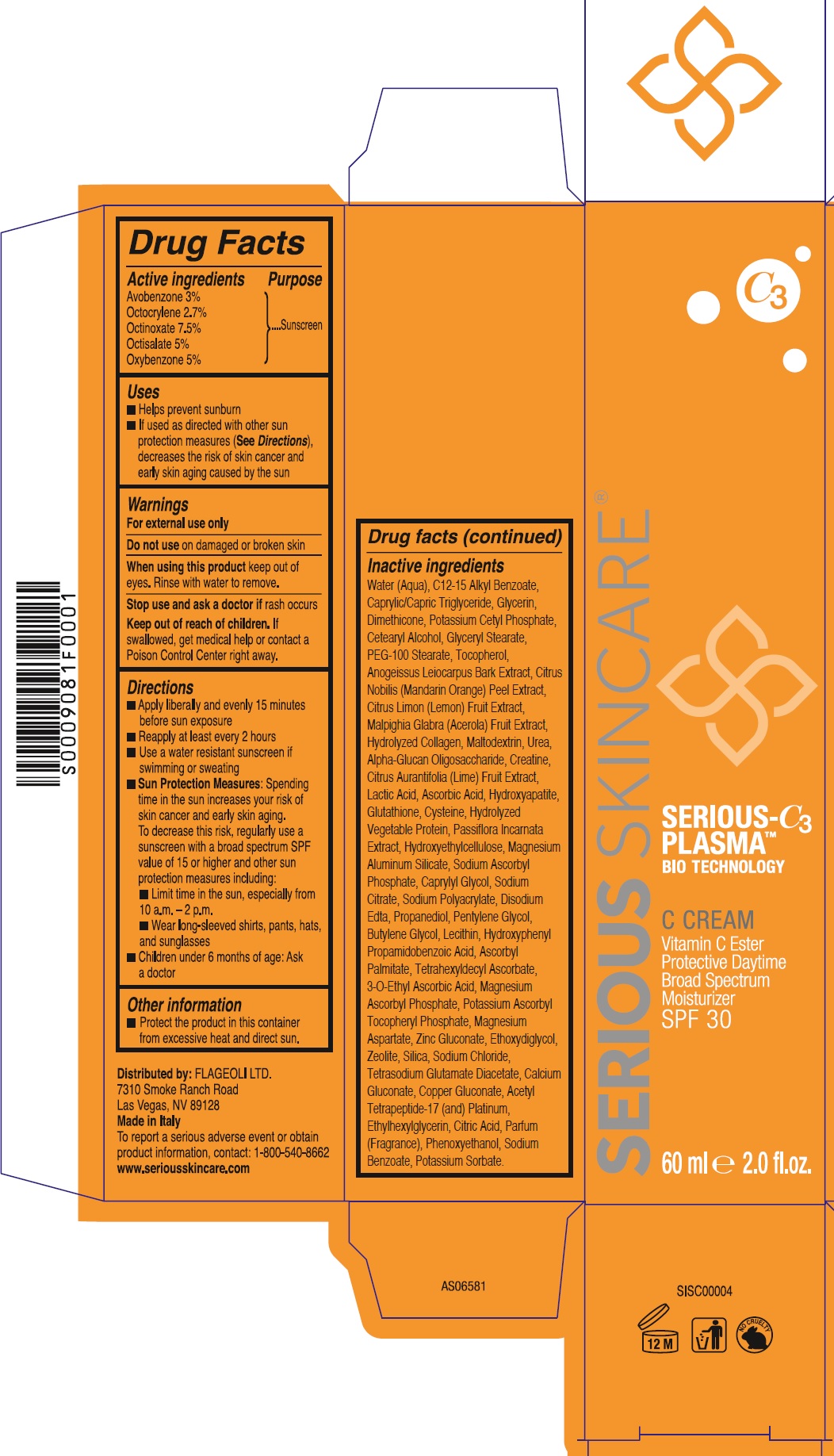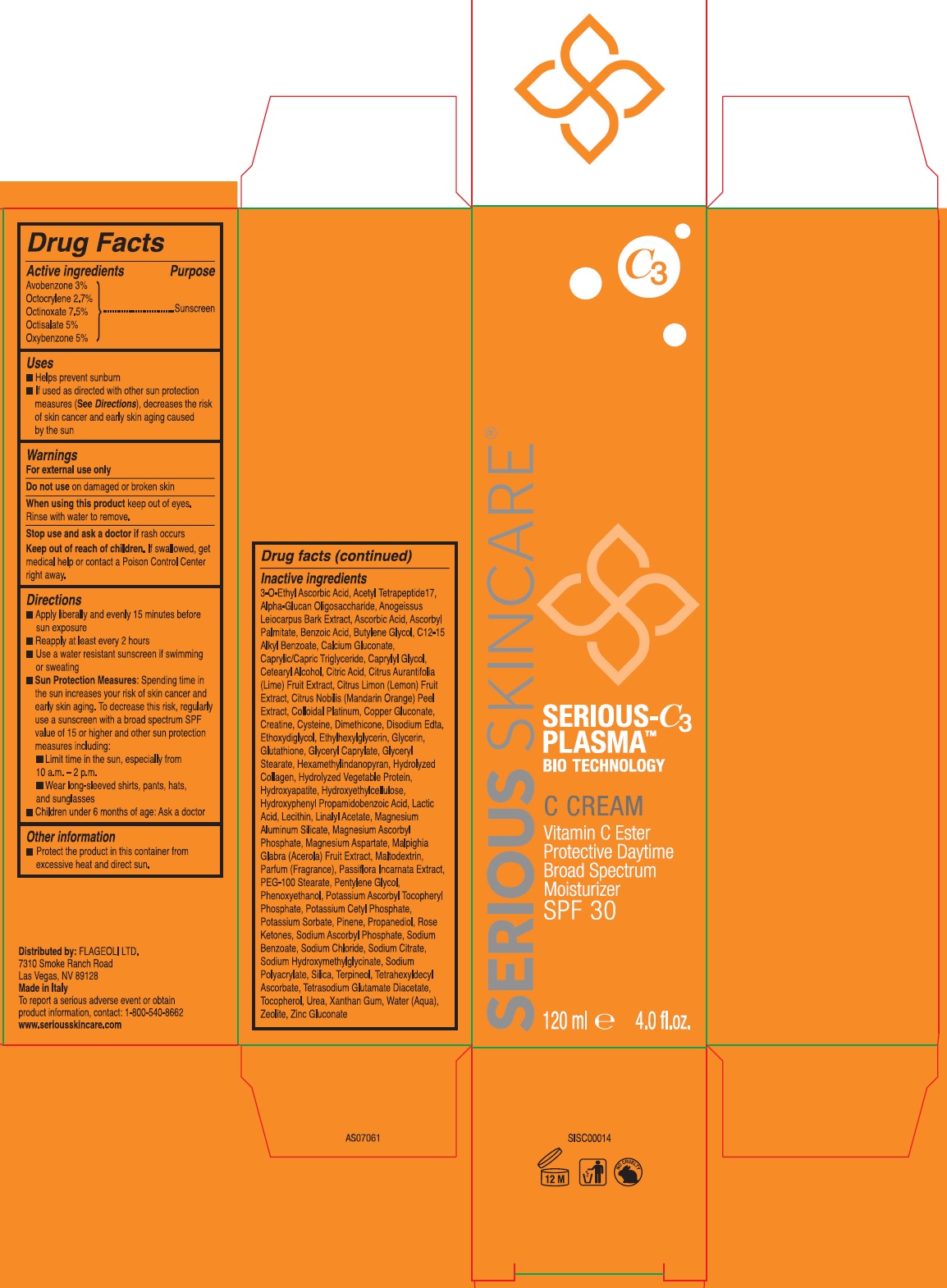 DRUG LABEL: Serious Skincare Serious-C3 Plasma Bio Technology C Cream SPF 30
NDC: 53755-120 | Form: CREAM
Manufacturer: Flageoli Limited
Category: otc | Type: HUMAN OTC DRUG LABEL
Date: 20260204

ACTIVE INGREDIENTS: AVOBENZONE 30 mg/1 mL; OCTOCRYLENE 27 mg/1 mL; OCTINOXATE 75 mg/1 mL; OCTISALATE 50 mg/1 mL; OXYBENZONE 50 mg/1 mL
INACTIVE INGREDIENTS: WATER; C12-15 ALKYL BENZOATE; MEDIUM-CHAIN TRIGLYCERIDES; GLYCERIN; DIMETHICONE; POTASSIUM CETYL PHOSPHATE; CETEARYL ALCOHOL; GLYCERYL MONOSTEARATE; PEG-100 MONOSTEARATE; TOCOPHEROL; ANOGEISSUS LEIOCARPUS BARK; TANGERINE PEEL; LEMON; MALPIGHIA GLABRA FRUIT; MALTODEXTRIN; UREA; .ALPHA.-GLUCAN OLIGOSACCHARIDE; CREATINE; LIME (CITRUS); LACTIC ACID; ASCORBIC ACID; HYDROXYAPATITE; GLUTATHIONE; CYSTEINE; HYDROXYETHYL CELLULOSE, UNSPECIFIED; MAGNESIUM ALUMINUM SILICATE; SODIUM ASCORBYL PHOSPHATE; CAPRYLYL GLYCOL; SODIUM CITRATE; EDETATE DISODIUM; PROPANEDIOL; PENTYLENE GLYCOL; BUTYLENE GLYCOL; HYDROXYPHENYL PROPAMIDOBENZOIC ACID; ASCORBYL PALMITATE; TETRAHEXYLDECYL ASCORBATE; 3-O-ETHYL ASCORBIC ACID; MAGNESIUM ASCORBYL PHOSPHATE; POTASSIUM ASCORBYL TOCOPHERYL PHOSPHATE; MAGNESIUM ASPARTATE; ZINC GLUCONATE; ETHOXYDIGLYCOL; ZEOLITE A; SODIUM CHLORIDE; TETRASODIUM GLUTAMATE DIACETATE; CALCIUM GLUCONATE; COPPER GLUCONATE; ETHYLHEXYLGLYCERIN; CITRIC ACID MONOHYDRATE; PHENOXYETHANOL; SODIUM BENZOATE; POTASSIUM SORBATE

Serious Skincare Serious-C3 Plasma Bio Technology C Cream SPF 30

Active ingredients

Avobenzone 3%
Octocrylene 2.7%
Octinoxate 7.5%
Octisalate 5%
Oxybenzone 5%

Purpose

Sunscreen

Uses

- Helps prevent sunburn
- If used as directed with other sun protection measures (See Directions), decreases the risk of skin cancer and early skin aging caused by the sun

Warnings

For external use only

Do not use

on damaged or broken skin

When using this product

keep out of eyes. Rinse with water to remove.

Stop use and ask a doctor if

rash occurs

Keep out of reach of children.

If swallowed, get medical help or contact a Poison Control Center right away.

Directions

- Apply liberally and evenly 15 minutes before sun exposure
- Reapply at least every 2 hours
- Use a water resistant sunscreen if swimming or sweating
- Sun Protection Measures:Spending time in the sun increases your risk of skin cancer and early skin aging. To decrease this risk, regularly use a sunscreen with a broad spectrum SPF value of 15 or higher and other sun protection measures including:
- Limit time in the sun, especially from 10a.m. – 2p.m.
- Wear long-sleeved shirts, pants, hats, and sunglasses
- Children under 6 months of age: Ask a doctor

Other information

Protect the product in this container from excessive heat and direct sun.

Inactive ingredients

Water (Aqua), C12-15 Alkyl Benzoate, Caprylic/Capric Triglyceride, Glycerin, Dimethicone, Potassium Cetyl Phosphate, Cetearyl Alcohol, Glyceryl Stearate, PEG-100 Stearate, Tocopherol, Anogeissus Leiocarpus Bark Extract, Citrus Nobilis (Mandarin Orange) Peel Extract, Citrus Limon (Lemon) Fruit Extract, Malpighia Glabra (Acerola) Fruit Extract,
Hydrolyzed Collagen, Maltodextrin, Urea, Alpha-Glucan Oligosaccharide, Creatine, Citrus Aurantifolia (Lime) Fruit Extract, Lactic Acid, Ascorbic Acid, Hydroxyapatite, Glutathione, Cysteine, Hydrolyzed Vegetable Protein, Passiflora Incarnata Extract, Hydroxyethylcellulose, Magnesium Aluminum Silicate, Sodium Ascorbyl Phosphate, Caprylyl Glycol, Sodium Citrate, Sodium Polyacrylate, Disodium Edta, Propanediol, Pentylene Glycol, Butylene Glycol, Lecithin, Hydroxyphenyl Propamidobenzoic Acid, Ascorbyl Palmitate, Tetrahexyldecyl Ascorbate, 3-O-Ethyl Ascorbic Acid, Magnesium Ascorbyl Phosphate, Potassium Ascorbyl Tocopheryl Phosphate, Magnesium Aspartate, Zinc Gluconate, Ethoxydiglycol, Zeolite, Silica, Sodium Chloride, Tetrasodium Glutamate Diacetate, Calcium Gluconate, Copper Gluconate, Acetyl Tetrapeptide-17 (and) Platinum, Ethylhexylglycerin, Citric Acid, Parfum (Fragrance), Phenoxyethanol, Sodium